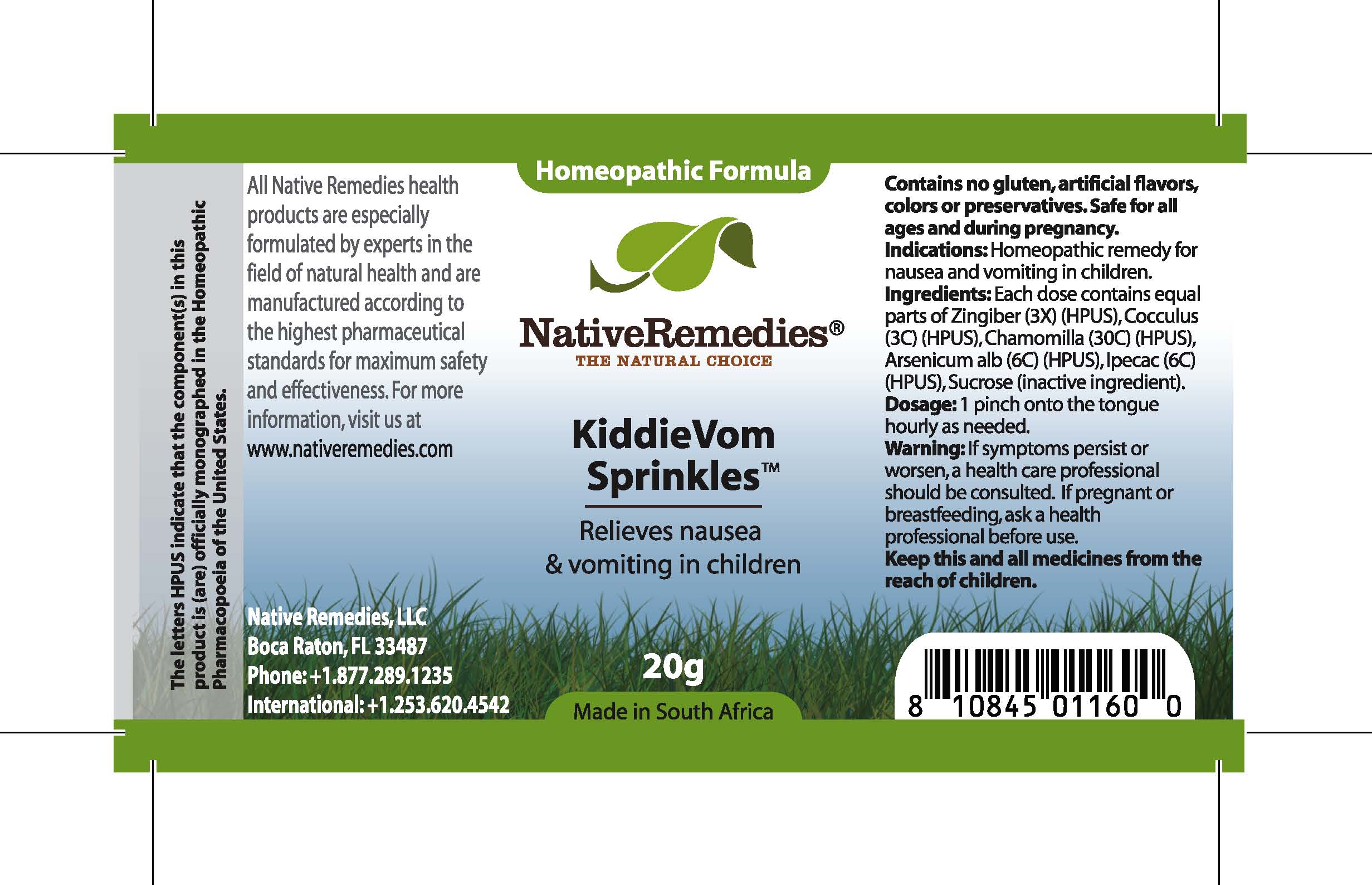 DRUG LABEL: KiddieVom
NDC: 68647-163 | Form: GRANULE
Manufacturer: Feelgood Health
Category: homeopathic | Type: HUMAN OTC DRUG LABEL
Date: 20100726

ACTIVE INGREDIENTS: CARDAMOM 3 [hp_X]/40 mg; JATEORHIZA CALUMBA ROOT 3 [hp_C]/40 mg; CHAMOMILE 30 [hp_C]/40 mg; ARSENIC TRIOXIDE 6 [hp_C]/40 mg; ASCLEPIAS CURASSAVICA 6 [hp_C]/40 mg
INACTIVE INGREDIENTS: SUCROSE 20000 mg/20000 mg

KIDDIEVOM

PURPOSE

Relieves nausea and vomiting in children

INDICATIONS AND USAGE

Indications: Homeopathic remedy for nausea and vomiting in children.

DOSAGE AND ADMINISTRATION

Dosage: 1 pinch onto the tongue hourly as needed.

GENERAL PRECAUTIONS

Caution: If symptoms persist or worsen, a health care professional should be consulted.

ACTIVE INGREDIENT

Ingredients: Each dose contains equal parts of Zingiber (3X) (HPUS), Cocculus (3C) (HPUS), Chamomilla (30C) (HPUS), Arsenicum alb (6C) (HPUS), Ipecac (6C) (HPUS)

Sucrose (inactive ingredient)

PREGNANCY

If pregnant or breastfeeding, ask a health professional before use.

WARNINGS

Contains no gluten, artificial flavors, colors or preservatives. Safe for all ages and during pregnancy.

PATIENT COUNSELING INFORMATION

All Native Remedies health products are especially formulated by experts in the field of natural health and are manufactured according to the highest pharmaceutical standards for maximum safety and effectiveness. For more information, visit us at www.nativeremedies.com

Distributed by

Native Remedies, LLC

6531 Park of Commerce Blvd.

Suite 160

Boca Raton, FL 33487

Phone: 1.877.289.1235

International: + 1.561.999.8857

The letters HPUS indicate that the component(s) in this product is (are) officially monographed in the Homeopathic Pharmacopoeia of the United States.

KEEP OUT OF REACH OF CHILDREN

Keep this and all medicines from the reach of children.